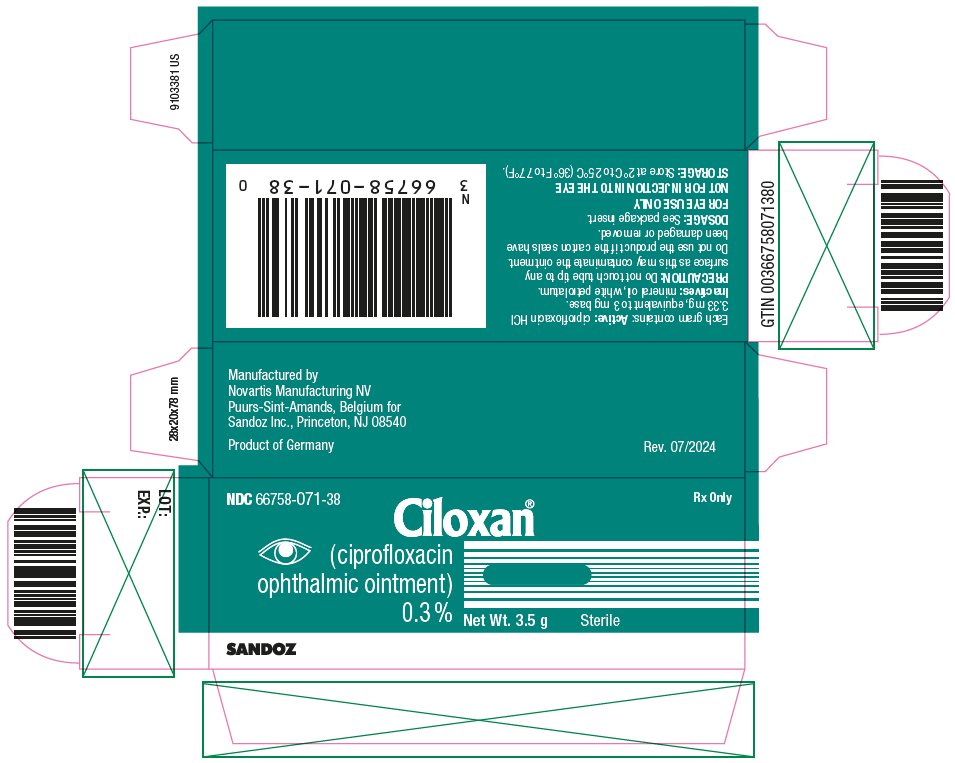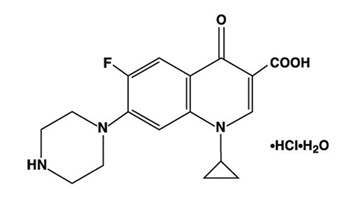 DRUG LABEL: CILOXAN
NDC: 66758-071 | Form: OINTMENT
Manufacturer: Sandoz Inc
Category: prescription | Type: HUMAN PRESCRIPTION DRUG LABEL
Date: 20240730

ACTIVE INGREDIENTS: CIPROFLOXACIN HYDROCHLORIDE 3 mg/1 g
INACTIVE INGREDIENTS: MINERAL OIL; PETROLATUM

CILOXAN® (ciprofloxacin ophthalmic ointment) 0.3%

Sterile Ophthalmic Ointment

DESCRIPTION:

CILOXAN® (ciprofloxacin ophthalmic ointment) 0.3% is a synthetic, sterile, multiple dose, antimicrobial for topical use. Ciprofloxacin is a fluoroquinolone antibacterial. It is available as the monohydrochloride monohydrate salt of 1-cyclopropyl-6-fluoro-1,4-dihydro-4-oxo-7-(1-piperazinyl)-3-quinolinecarboxylic acid. Ciprofloxacin is a faint to light yellow crystalline powder with a molecular weight of 385.82 g/mol. Its empirical formula is C17H18FN3O3•HCl•H2O and its chemical structure is as follows:

Ciprofloxacin differs from other quinolones in that it has a fluorine atom at the 6-position, a piperazine moiety at the 7-position, and a cyclopropyl ring at the 1-position.

Each gram of CILOXAN® (ciprofloxacin ophthalmic ointment) 0.3% contains: Active: ciprofloxacin HCl 3.33 mg equivalent to 3 mg base. Inactives: mineral oil, white petrolatum.

CLINICAL PHARMACOLOGY:

Systemic Absorption: Absorption studies in humans with the ciprofloxacin ointment have not been conducted, however, based on studies with ciprofloxacin solution, 0.3%, mean maximal concentrations are expected to be less than 2.5 ng/mL.

Microbiology: Ciprofloxacin has in vitro activity against a wide range of gram-negative and gram-positive organisms. The bactericidal action of ciprofloxacin results from interference with the enzyme DNA gyrase which is needed for the synthesis of bacterial DNA.

Ciprofloxacin has been shown to be active against most strains of the following microorganisms both in vitro and in clinical infections (see INDICATIONS AND USAGE section).

Aerobic gram-positive microorganisms:
Staphylococcus aureus (methicillin-susceptible strains)
Staphylococcus epidermidis (methicillin-susceptible strains)
Streptococcus pneumoniae
Streptococcus Viridans Group

Aerobic gram-negative microorganisms:
Haemophilus influenzae

The following in vitro data are available; but their clinical significance in ophthalmologic infections is unknown. The safety and effectiveness of ciprofloxacin in treating conjunctivitis due to these microorganisms have not been established in adequate and well-controlled trials.

The following organisms are considered susceptible when evaluated using systemic breakpoints. However, a correlation between the in vitro systemic breakpoint and ophthalmological efficacy has not been established. Ciprofloxacin exhibits in vitro minimal inhibitory concentrations (MIC’s) of 1 mcg/mL or less (systemic susceptible breakpoint) against most (greater than or equal to 90%) strains of the following ocular pathogens.

Aerobic gram-positive microorganisms:
Bacillus species
Corynebacterium species
Staphylococcus haemolyticus
Staphylococcus hominis

Aerobic gram-negative microorganisms:
Acinetobacter calcoaceticus
Enterobacter aerogenes
Escherichia coli
Haemophilus parainfluenzae
Klebsielle pneumoniae
Moraxella catarrhalis
Neisseria gonorrhoeae
Proteus mirabilis
Pseudomonas aeruginosa
Serratia marcesens

Most strains of Burkholderia cepacia and some strains of Stenotrophomonas maltophilia are resistant to ciprofloxacin as are most anaerobic bacteria, including Bacteroides fragilis and Clostridium difficile.

The minimal bactericidal concentration (MBC) generally does not exceed the minimal inhibitory concentration (MIC) by more than a factor of 2. Resistance to ciprofloxacin in vitro usually develops slowly (multiple-step mutation). Ciprofloxacin does not cross-react with other antimicrobial agents such as beta-lactams or aminoglycosides; therefore, organisms resistant to these drugs may be susceptible to ciprofloxacin. Organisms resistant to ciprofloxacin may be susceptible to beta-lactams or aminoglycosides.

Clinical Studies: In multi-center clinical trials, approximately 75% of the patients with signs and symptoms of bacterial conjunctivitis and positive conjunctival cultures were clinically cured and approximately 80% had presumed pathogens eradicated by the end of treatment (Day 7).

INDICATIONS AND USAGE:

CILOXAN® (ciprofloxacin ophthalmic ointment) 0.3% is indicated for the treatment of bacterial conjunctivitis caused by susceptible strains of the microorganisms listed below:

Gram-Positive:
  Staphylococcus aureus
  Staphylococcus epidermidis
  Streptococcus pneumoniae
  Streptococcus Viridans Group

Gram-Negative:
Haemophilus influenzae

CONTRAINDICATIONS:

A history of hypersensitivity to ciprofloxacin or any other component of the medication is a contraindication to its use. A history of hypersensitivity to other quinolones may also contraindicate the use of ciprofloxacin.

WARNINGS:

FOR EYE USE ONLY

NOT FOR INJECTION INTO THE EYE

Serious and occasionally fatal hypersensitivity (anaphylactic) reactions, some following the first dose, have been reported in patients receiving systemic quinolone therapy. Some reactions were accompanied by cardiovascular collapse, loss of consciousness, tingling, pharyngeal or facial edema, dyspnea, urticaria, and itching. Only a few patients had a history of hypersensitivity reactions. Serious anaphylactic reactions require immediate emergency treatment with epinephrine and other resuscitation measures, including oxygen, intravenous fluids, intravenous antihistamines, corticosteroids, pressor amines, and airway management, as clinically indicated.

PRECAUTIONS:

GENERAL PRECAUTIONS

General: As with other antibacterial preparations, prolonged use of ciprofloxacin may result in overgrowth of nonsusceptible organisms, including fungi. If superinfection occurs, appropriate therapy should be initiated. Whenever clinical judgment dictates, the patient should be examined with the aid of magnification, such as slit lamp biomicroscopy and, where appropriate, fluorescein staining. Ciprofloxacin should be discontinued at the first appearance of a skin rash or any other sign of hypersensitivity reaction. Ophthalmic ointments may retard corneal healing and cause visual blurring. Patients should be advised not to wear contact lenses if they have signs and symptoms of bacterial conjunctivitis.

PATIENT COUNSELING INFORMATION

Information for Patients: Do not touch tip to any surface as this may contaminate the ointment. Do not use the product if the imprinted carton seals have been damaged, or removed.

DRUG INTERACTIONS

Drug Interactions: Specific drug interaction studies have not been conducted with ophthalmic ciprofloxacin. However, the systemic administration of some quinolones has been shown to elevate plasma concentrations of theophylline, interfere with the metabolism of caffeine, enhance the effects of the oral anticoagulant, warfarin, and its derivatives, and has been associated with transient elevations in serum creatinine in patients receiving cyclosporine concomitantly.

CARCINOGENESIS AND MUTAGENESIS AND IMPAIRMENT OF FERTILITY

Carcinogenesis, Mutagenesis, Impairment of Fertility: Eight in vitro mutagenicity tests have been conducted with ciprofloxacin and the test results are listed below:

- Salmonella/Microsome Test (Negative)
- E. coli DNA Repair Assay (Negative)
- Mouse Lymphoma Cell Forward Mutation Assay (Positive)
- Chinese Hamster V79 Cell HGPRT Test (Negative)
- Syrian Hamster Embryo Cell Transformation Assay (Negative)
- Saccharomyces cerevisiae Point Mutation Assay (Negative)
- Saccharomyces cerevisiae Mitotic Crossover and Gene Conversion Assay (Negative)
- Rat Hepatocyte DNA Repair Assay (Positive)

Thus, two of the eight tests were positive, but the results of the following three in vivo test systems gave negative results:

- Rat Hepatocyte DNA Repair Assay
- Micronucleus Test (Mice)
- Dominant Lethal Test (Mice)

Long-term carcinogenicity studies in mice and rats have been completed. After daily oral dosing for up to two years, there is no evidence that ciprofloxacin had any carcinogenic or tumorigenic effects in these species.

PREGNANCY

Pregnancy: Reproduction studies have been performed in rats and mice at doses up to six times the usual daily human oral dose and have revealed no evidence of impaired fertility or harm to the fetus due to ciprofloxacin. In rabbits, as with most antimicrobial agents, ciprofloxacin (30 and 100 mg/kg orally) produced gastrointestinal disturbances resulting in maternal weight loss and an increased incidence of abortion. No teratogenicity was observed at either dose. After intravenous administration, at doses up to 20 mg/kg, no maternal toxicity was produced and no embryotoxicity or teratogenicity was observed. There are no adequate and well controlled studies in pregnant women. CILOXAN® (ciprofloxacin ophthalmic ointment) 0.3% should be used during pregnancy only if the potential benefit justifies the potential risk to the fetus.

NURSING MOTHERS

Nursing Mothers: It is not known whether topically applied ciprofloxacin is excreted in human milk. However, it is known that orally administered ciprofloxacin is excreted in the milk of lactating rats and oral ciprofloxacin has been reported in human breast milk after a single 500 mg dose. Caution should be exercised when CILOXAN® (ciprofloxacin ophthalmic ointment) 0.3% is administered to a nursing mother.

PEDIATRIC USE

Pediatric Use: Safety and effectiveness of CILOXAN® (ciprofloxacin ophthalmic ointment) 0.3% in pediatric patients below the age of two years have not been established. Although ciprofloxacin and other quinolones may cause arthropathy in immature Beagle dogs after oral administration, topical ocular administration of ciprofloxacin to immature animals did not cause any arthropathy and there is no evidence that the ophthalmic dosage form has any effect on the weight bearing joints.

GERIATRIC USE

Geriatric Use: No overall clinical differences in safety or effectiveness have been observed between the elderly and other adult patients.

ADVERSE REACTIONS:

The following adverse reactions (incidences) were reported in 2% of the patients in clinical studies for CILOXAN® (ciprofloxacin ophthalmic ointment) 0.3%: discomfort and keratopathy. Other reactions associated with ciprofloxacin therapy occurring in less than 1% of patients included allergic reactions, blurred vision, corneal staining, decreased visual acuity, dry eye, edema, epitheliopathy, eye pain, foreign body sensation, hyperemia, irritation, keratoconjunctivitis, lid erythema, lid margin hyperemia, photophobia, pruritus, and tearing. Systemic adverse reactions related to ciprofloxacin therapy occurred at an incidence below 1% and included dermatitis, nausea and taste perversion.

DOSAGE AND ADMINISTRATION:

Apply a ½ inch ribbon into the conjunctival sac three times a day on the first two days, then apply a ½ inch ribbon two times a day for the next five days.

HOW SUPPLIED:

3.5 g STERILE ointment supplied in an aluminum tube with a white polyethylene tip and white polyethylene cap.

3.5 g NDC 66758-071-38

Storage: Store at 2°C to 25°C (36°F to 77°F).

ANIMAL PHARMACOLOGY:

Ciprofloxacin and related drugs have been shown to cause arthropathy in immature animals of most species tested following oral administration. However, a one month topical ocular study using immature Beagle dogs did not demonstrate any articular lesions.

Manufactured by

Novartis Manufacturing NV

Puurs-Sint-Amands, Belgium for

Sandoz Inc., Princeton, NJ 08540

Rev: 07/2024

9103380 US

PRINCIPAL DISPLAY PANEL

NDC 66758-071-38 Rx Only

Ciloxan®

(ciprofloxacin

ophthalmic ointment)

0.3%

Net Wt. 3.5 g Sterile

SANDOZ